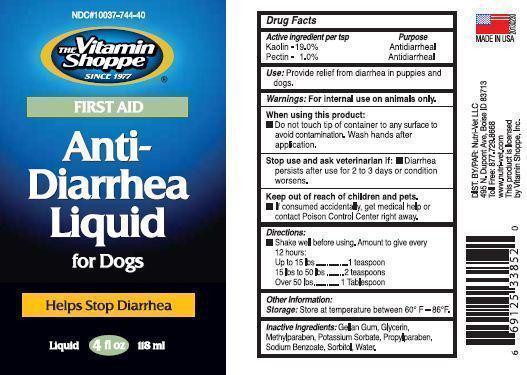 DRUG LABEL: Nutri Vet
NDC: 10037-744 | Form: LIQUID
Manufacturer: Nutri-Vet LLC
Category: animal | Type: OTC ANIMAL DRUG LABEL
Date: 20130429

ACTIVE INGREDIENTS: KAOLIN 19 g/100 mL; PECTIN 1 g/100 mL
INACTIVE INGREDIENTS: GELLAN GUM (LOW ACYL); GLYCERIN; METHYLPARABEN; POTASSIUM SORBATE; PROPYLPARABEN; SODIUM BENZOATE; SORBITOL; WATER

Drug Facts

Active ingredient per tsp

Kaolin 19.0%

Pectin 1.0 %

Purpose

Antidiarrheal

INDICATIONS AND USAGE

Use: Provide relief from diarrhea in puppies and dogs.

Warnings: For external use on animals only.

When using this product:

Do not touch tip of container to any surface to avoid contamination. Wash hands after application.

Stop use and ask veterinarian if: Diarrhea persists after use for 2 to 3 days or condition worsens.

Keep out of reach of children and pets. If consumed accidently, get medical help

or contact Poison Control Center right away.

Directions:

Shake well before using. Amount to give every 12 hours:

Up to 15 lbs --- 1 teaspoon

15 lbs to 50 lbs --- 2 teaspoons

Over 50 lbs--- 1 Tablespoon

Other information:

Storage: Store at temperature between 60 F - 86 F

INACTIVE INGREDIENT

Inactive Ingredients: Gellan Gum, Glycerin, Methylparaben, Potassium Sorbate, Propylparaben, Sodium Benzoate, Sorbitol, Water